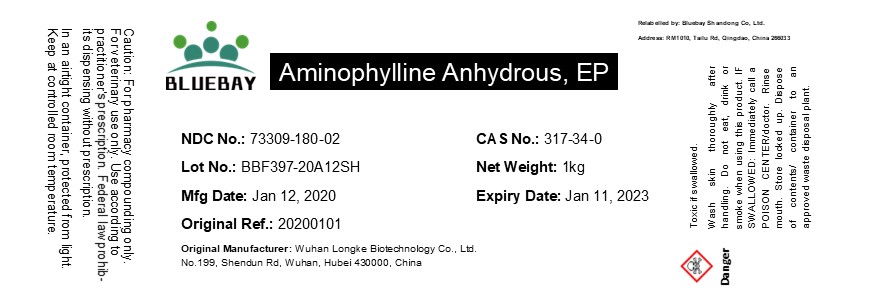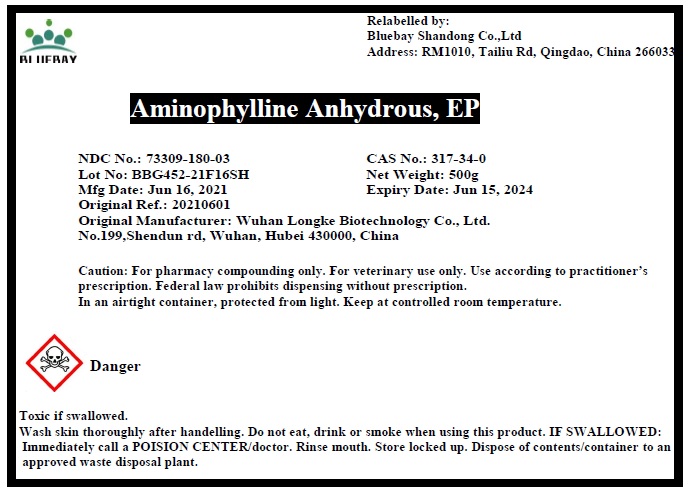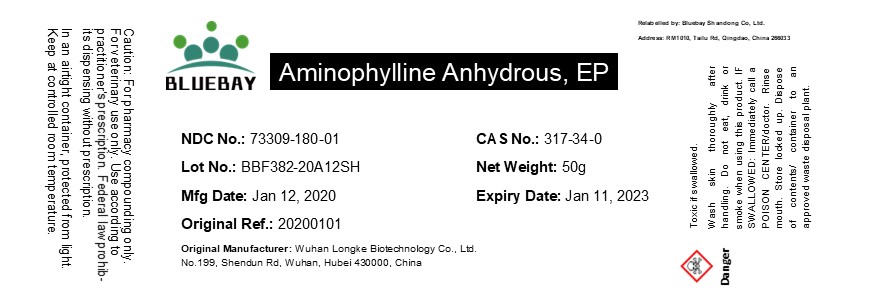 DRUG LABEL: Aminophylline Anhydrous
NDC: 73309-180 | Form: POWDER
Manufacturer: BLUEBAY SHANDONG CO.,LTD
Category: other | Type: BULK INGREDIENT
Date: 20211020

ACTIVE INGREDIENTS: AMINOPHYLLINE 1 g/1 g

Aminophylline Anhydrous